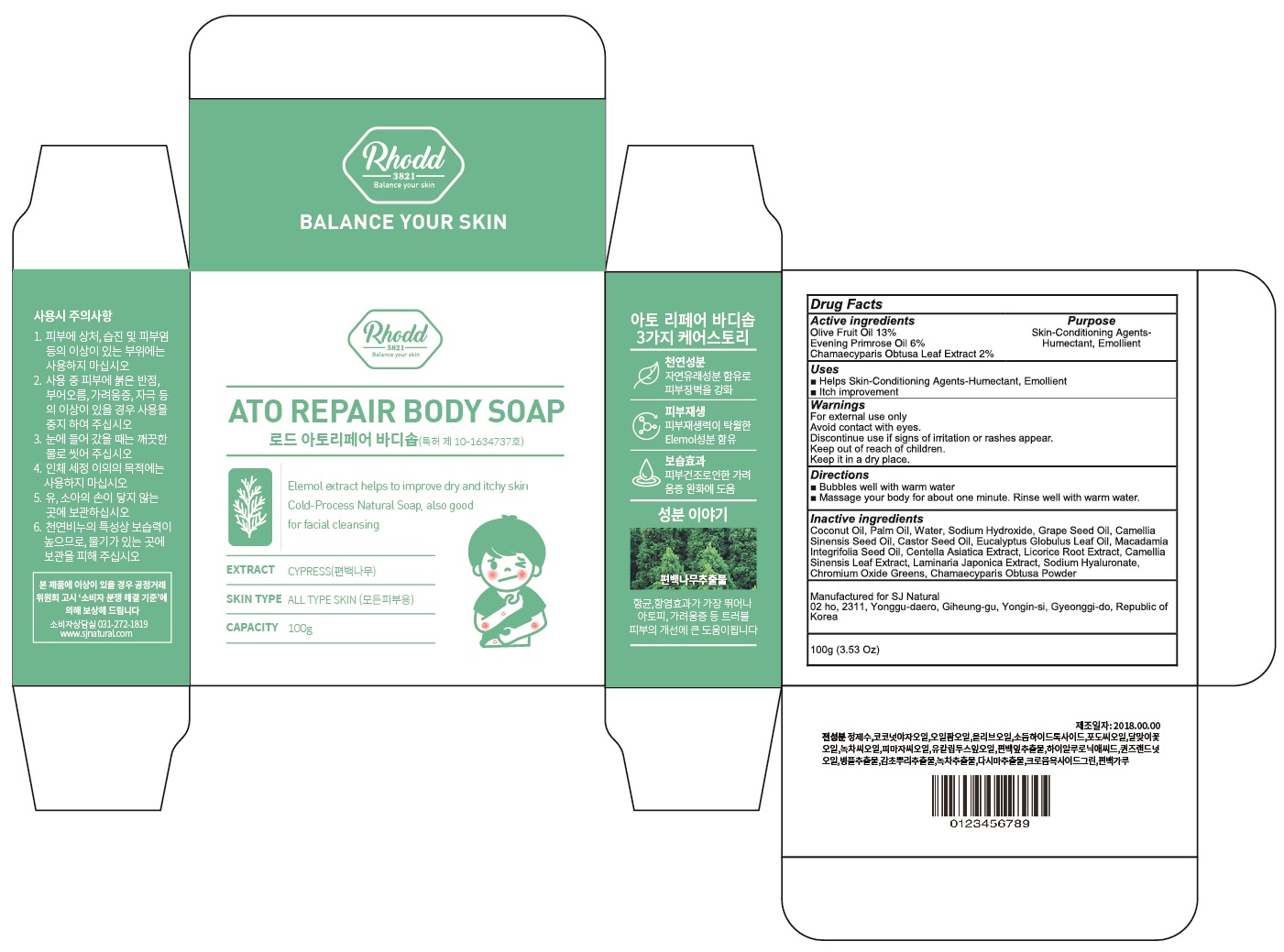 DRUG LABEL: RHODD ATO REPAIR BODY SO AP
NDC: 72535-010 | Form: SOAP
Manufacturer: SJ NATURAL
Category: otc | Type: HUMAN OTC DRUG LABEL
Date: 20180904

ACTIVE INGREDIENTS: OLIVE OIL 13.0 g/100 g; EVENING PRIMROSE OIL 6.0 g/100 g; CHAMAECYPARIS OBTUSA LEAF 2.0 g/100 g
INACTIVE INGREDIENTS: COCONUT OIL; PALM OIL

ACTIVE INGREDIENT

Active ingredients: Olive Fruit Oil 13%, Evening Primrose Oil 6%, Chamaecyparis Obtusa Leaf Extract 2%

INACTIVE INGREDIENT

Inactive ingredients:

Coconut Oil, Palm Oil, Water, Sodium Hydroxide, Grape Seed Oil, Camellia Sinensis Seed Oil, Castor Seed Oil, Eucalyptus Globulus Leaf Oil, Macadamia Integrifolia Seed Oil, Centella Asiatica Extract, Licorice Root Extract, Camellia Sinensis Leaf Extract, Laminaria Japonica Extract, Sodium Hyaluronate, Chromium Oxide Greens, Chamaecyparis Obtusa Powder

PURPOSE

Purpose: Skin-Conditioning Agents-Humectant, Emollient

WARNINGS

For external use only

Avoid contact with eyes.

Discontinue use if signs of irritation or rashes appear.

Keep out of reach of children.

Keep it in a dry place.

KEEP OUT OF REACH OF CHILDREN

Uses

- Helps Skin-Conditioning Agents-Humectant, Emollient

- Itch improvement

Directions

- Bubbles well with warm water

- Massage your body for about one minute. Rinse well with warm water.